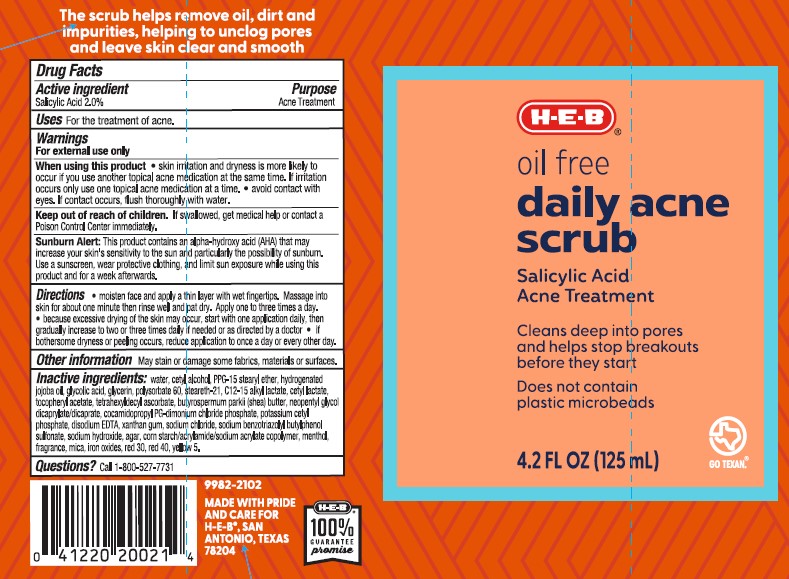 DRUG LABEL: H.E.B. Oil Free Daily Acne Scrub
NDC: 37808-342 | Form: CREAM
Manufacturer: H.E.B
Category: otc | Type: HUMAN OTC DRUG LABEL
Date: 20241015

ACTIVE INGREDIENTS: SALICYLIC ACID 20 mg/1 mL
INACTIVE INGREDIENTS: WATER; EDETATE DISODIUM; CETYL ALCOHOL; PPG-15 STEARYL ETHER; COCAMIDOPROPYL PG-DIMONIUM CHLORIDE PHOSPHATE; C12-15 ALKYL LACTATE; GLYCOLIC ACID; GLYCERIN; POLYSORBATE 60; STEARETH-21; FD&C YELLOW NO. 5; FD&C RED NO. 40; .ALPHA.-TOCOPHEROL ACETATE; TETRAHEXYLDECYL ASCORBATE; SHEA BUTTER; CETYL LACTATE; NEOPENTYL GLYCOL DICAPRYLATE/DICAPRATE; POTASSIUM CETYL PHOSPHATE; XANTHAN GUM; SODIUM CHLORIDE; SODIUM BENZOTRIAZOLYL BUTYLPHENOL SULFONATE; SODIUM HYDROXIDE; AGAR; MENTHOL; MICA; D&C RED NO. 30; FERRIC OXIDE RED; HYDROGENATED JOJOBA OIL

H.E.B. Oil Free Daily Acne Scrub

Active ingredient

Salicylic Acid 2.0%

Purpose

Acne Treatment

Uses

For the treatment of acne.

Warnings

For external use only

When using this product

- skin irritation and dryness is more likely to occur if you use another topocal acne medication at the same time. If irritation occurs, only use one topicla acne medication at a time.
- avoid contact with eyes. If contact occurs, flush thoroughly with water.

Keep out of reach of children.

If swallowed, get medical help or contact a Poison Control Center right away.

Sunburn Alert:

This product contains an alpha-hydroxy acid (AHA) that may increase skin's sensitivity to the sun and particularly thepossibility of sunburn. Use a sunscreen, wear protective clothing, and limit sun exposure while using this product and for two weeks afterwards.

Directions

- cover the entire affected area with a think layer and rinse thoroughly one to three times daily
- because excessive drying of the skin may occur, start with one application daily, then gradually increase to two or three times daily if needed or as directed by a doctor
- if bothersome dryness or peeling occurs, reduce application to once a day or every other day.

Other information

- may stain or damage some fabrics, materilas, or surfaces

Inactive ingredients

water, cetyl alcohol, PPG-15 stearyl ether, hydrogenated jojoba oil, glycolic acid, glycerin, polysorbate 60, steareth-21, C12-15 alkyl lactate, cetyl lactate, tocopheryl acetate, tetrahexyldecyl ascorbate, butyrospermum parkii (shea butter), cetyl lactate, neopentyl glycol dicaprylate/dicaprate, cocamidopropyl PG-dimonium chloride phosphate, potassium cetyl phosphate, disodium EDTA, xanthan gum, sodium chloride, sodium benzotriazolyl butylphenol sulfonate, sodium hydroxide, agar, corn starch/acrylamide/sodium copolymer, menthol, fragrance, mica, iron oxide, red 30, red 40, yellow 5.